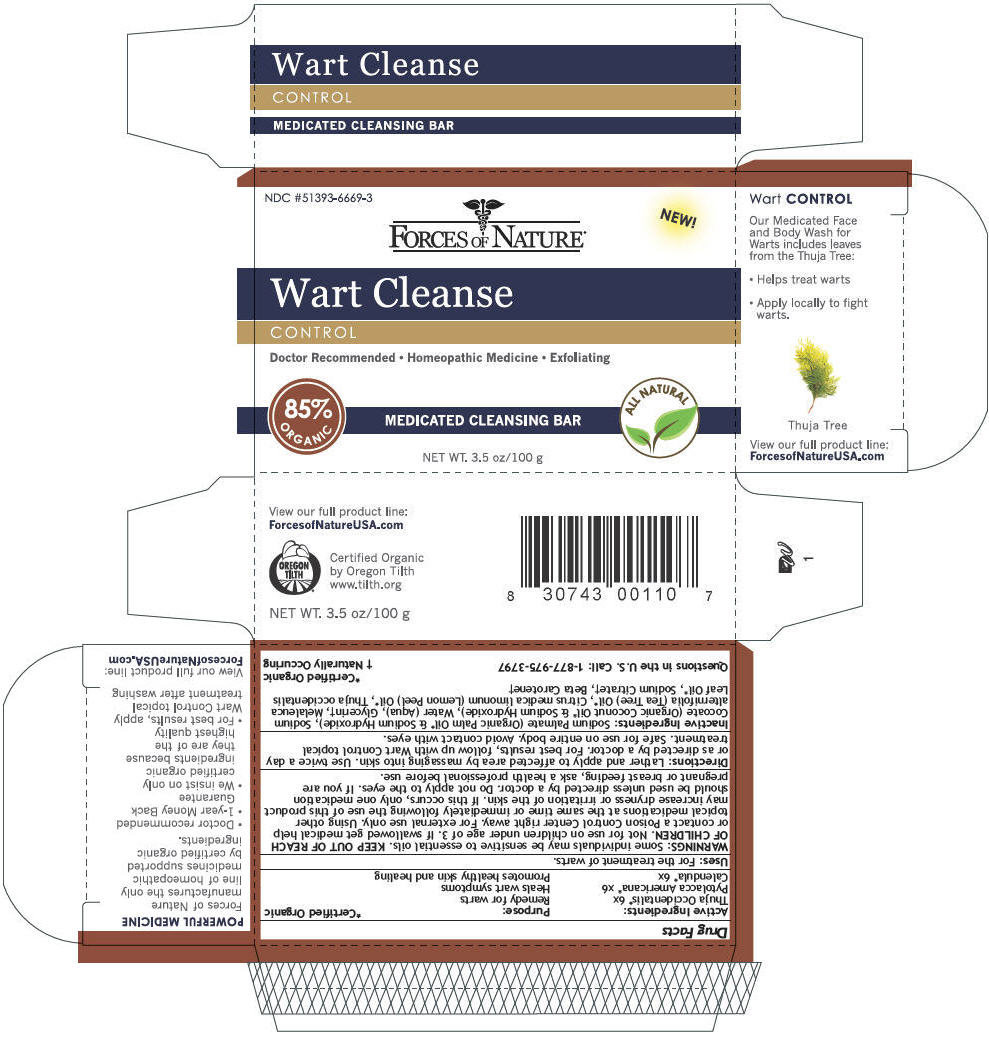 DRUG LABEL: Wart Cleanse
NDC: 51393-6669 | Form: SOAP
Manufacturer: Forces of Nature
Category: homeopathic | Type: HUMAN OTC DRUG LABEL
Date: 20131031

ACTIVE INGREDIENTS: THUJA OCCIDENTALIS BARK 6 [hp_X]/100 g; PHYTOLACCA AMERICANA ROOT 6 [hp_X]/100 g; CALENDULA OFFICINALIS FLOWERING TOP 6 [hp_X]/100 g
INACTIVE INGREDIENTS: Sodium Palmate; Sodium Cocoate; Water; Glycerin; TEA TREE OIL; LEMON OIL; CEDAR LEAF OIL; Sodium Citrate; .BETA.-CAROTENE

Wart Cleanse

Drug Facts

ACTIVE INGREDIENT

Active Ingredients: | Purpose:
Thuja Occidentalis [Certified Organic] 6x | Remedy for warts
Pytolacca Americana x6 | Heals wart symptoms
Calendula 6x | Promotes healthy skin and healing

Uses

For the treatment of warts.

WARNINGS

Some individuals may be sensitive to essential oils.

KEEP OUT OF REACH OF CHILDREN. Not for use on children under age of 3. If swallowed get medical help or contact a Poison Control Center right away.

WHEN USING

For external use only. Using other topical medications at the same time or immediately following the use of this product may increase dryness or irritation of the skin. If this occurs, only one medication should be used unless directed by a doctor.

Do not apply to the eyes.

PREGNANCY OR BREAST FEEDING

If you are pregnant or breast feeding, ask a health professional before use.

Directions

Lather and apply to affected area by massaging into skin. Use twice a day or as directed by a doctor. For best results, follow up with Wart Control topical treatment. Safe for use on entire body. Avoid contact with eyes.

Inactive Ingredients

Sodium Palmate (Organic Palm Oil [Certified Organic] & Sodium Hydroxide), Sodium Cocoate (Organic Coconut Oil & Sodium Hydroxide), Water (Aqua), Glycerin [Naturally Occuring] , Melaleuca alternifolia (Tea Tree) Oil, Citrus medica limonum (Lemon Peel) Oil, Thuja occidentalis Leaf Oil, Sodium Citrate, Beta Carotene

QUESTIONS

Questions in the U.S. Call: 1-877-975-3797

PRINCIPAL DISPLAY PANEL - 100 g Box

NDC #51393-6669-3

FORCES OF NATURE®

NEW!

Wart Cleanse

CONTROL

Doctor Recommended • Homeopathic Medicine • Exfoliating

85%
ORGANIC

MEDICATED CLEANSING BAR

ALL NATURAL

NET WT. 3.5 oz/100 g